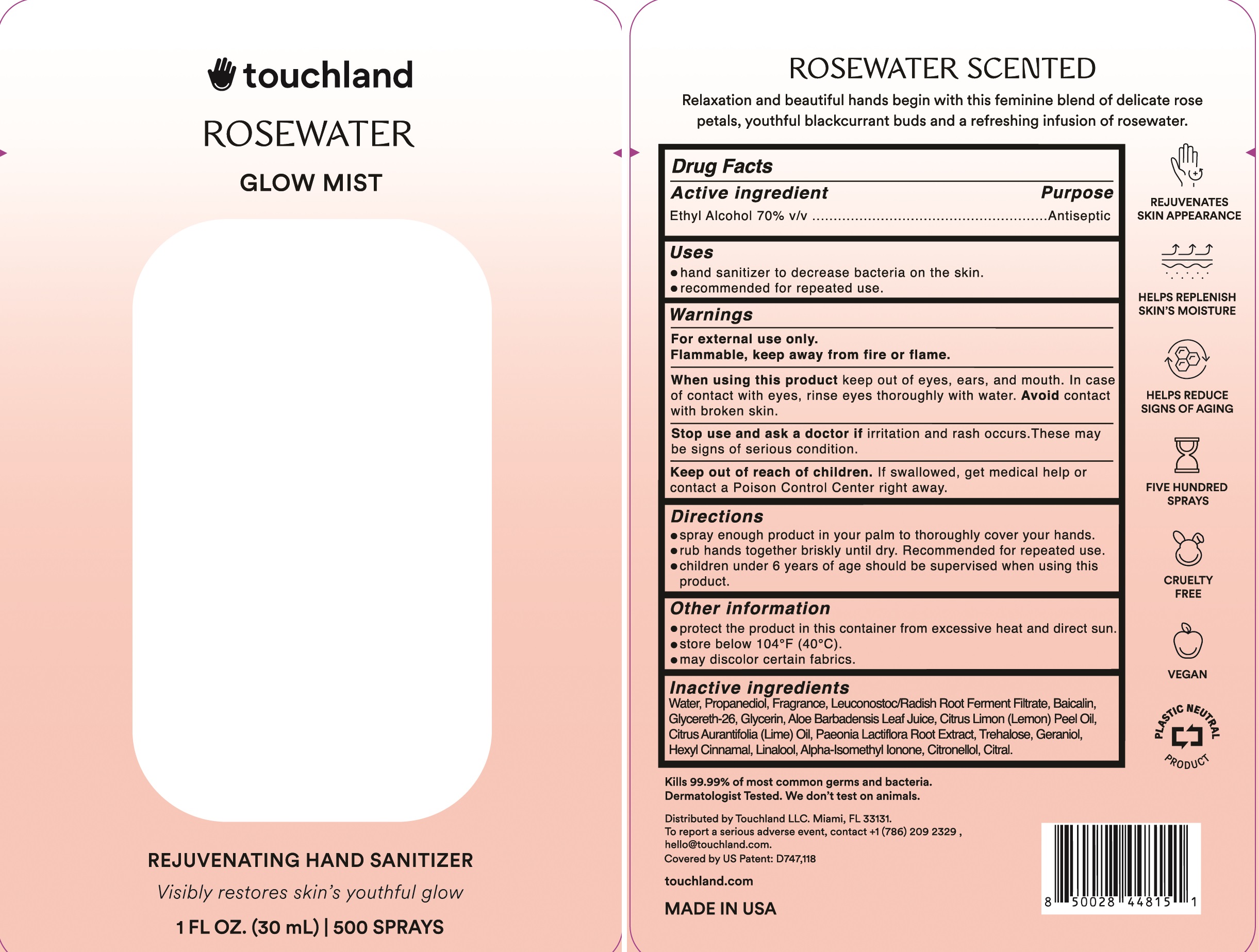 DRUG LABEL: Touchland Glow Mist Hand Sanitizer Rosewater
NDC: 72033-113 | Form: SPRAY
Manufacturer: Touchland LLC
Category: otc | Type: HUMAN OTC DRUG LABEL
Date: 20231214

ACTIVE INGREDIENTS: ALCOHOL 0.7 mL/1 mL
INACTIVE INGREDIENTS: GERANIOL; .BETA.-CITRONELLOL, (R)-; CITRAL; GLYCERIN; GLYCERETH-26; LEMON OIL; ALOE VERA LEAF; LEUCONOSTOC/RADISH ROOT FERMENT FILTRATE; WATER; LIME OIL; PROPANEDIOL; BAICALIN; TREHALOSE; PAEONIA LACTIFLORA ROOT; .ALPHA.-HEXYLCINNAMALDEHYDE; LINALOOL, (+)-; ISOMETHYL-.ALPHA.-IONONE

Touchland Hand Sanitizer - Rosewater

Active ingredient

Ethyl Alcohol 70% v/v

Purpose

Antiseptic

Use

Hand sanitizer to decrease bacteria on the skin
recommended for repeated use

Warnings

For external use only

Flammable, keep away from fire and flame

When using this product

keep out of eyes, ears, and mouth. In case of contact with eyes, rinse eyes thoroughly with water. Avoid contact with broken skin.

Stop use and ask a doctor if

- irritation and rash occurs. These may be signs of serious condition.

Keep out of reach of children

If swallowed, get medical help or contact an Poison Control Center right away.

Directions

- spray enough product in your palm to thoroughly cover your hands.
- rub hands togehter briskly until dry. Recommended for repeated use.
- children under 6 years of age should be supervised when using this product

Other Information

- protect the product in this container from excessive heat and direct sun
- store below 104F (40C)
- may discolor certain fabrics

Inactive ingredients

Water, Propanediol, Fragrance, Leuconostoc/Radish Root Ferment Filtrate, Baicalin, Glycereth-26, Glycerin, Aloe Barbadensis Leaf Juice, Citrus Limon (Lemon) Peel Oil, Citrus Aurantifolia (Lime) Oil, Paeonia Lactiflora Root Extract, Trehelose, Geraniol, Hexyl Cinnamal, Linalool, Alpha-Isomethyl Ionone, Citronellol, Citral